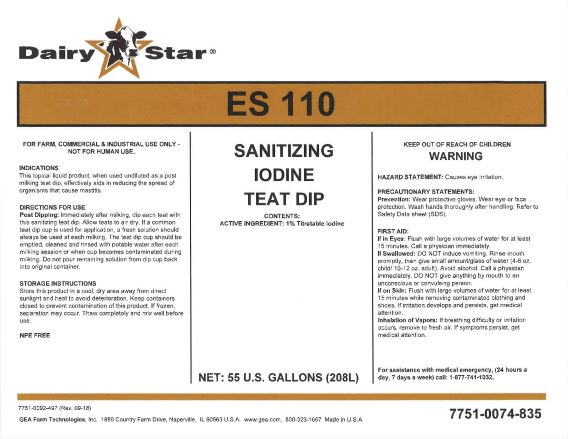 DRUG LABEL: Dairy Star EconoStar 110 Sanitizing Teat Dip
NDC: 51070-4040 | Form: LIQUID
Manufacturer: GEA Farm Technologies, Inc.
Category: animal | Type: OTC ANIMAL DRUG LABEL
Date: 20191024

ACTIVE INGREDIENTS: Iodine 1 g/100 g

EconoStar 110

ACTIVE INGREDIENT

CONTENTS:

ACTIVE INGREDIENT: 1% Titratable iodine

Net: 15 U.S. Gallons (56.7L)

KEEP OUT OF REACH OF CHILDREN

WARNING

PRECAUTIONS

HAZARD STATEMENT:

Causes eye irritation.

PRECAUTIONARY STATEMENTS

Prevention: Wear protective gloves. Wear eye or face protection. Wash hands thoroughly after handling. Refer to Safety Data Sheet (SDS).

USER SAFETY WARNINGS

FIRST AID

If in Eyes: Flush with large volumes of water for at least 15 minutes. Call a physician immediately.
If Swallowed: DO NOT induce vomiting. Rinse mouth promptly, then give small amount/glass of water (4-6 oz. child / 10-12 oz. adult). Avoid alcohol. Call a physician immediately. DO NOT give anything by mouth to an unconscious or convulsing person.
If on Skin: Flush with large volumes of water for at least 15 minutes while removing contaminated clothing and shoes. If irritation develops and persists, get medical attention.
Inhalation of Vapors: If breathing difficulty or irritation occurs, remove to fresh air. If symptoms persist, get medical attention.

For assistance with medical emergency, (24 hours a day, 7 days a week) call: 1-877-741-1032.

FOR FARM, COMMERCIAL & INDUSTRIAL USE ONLY

- NOT FOR HUMAN USE

INDICATIONS

This topical liquid product, when used undiluted as a post milking teat dip, effectively aids in reducing the spread of organisms that cause mastitis.

DOSAGE AND ADMINISTRATION

DIRECTIONS FOR USE

Post Dipping: Immediately after milking, dip each teat with this sanitizing teat dip. Allow teats to air dry. If a common teat dip cup is used for application, a fresh solution should always be used at each milking. The teat dip cup should be emptied, cleaned and rinsed with potable water after each milking session or when cup becomes contaminated during milking. Do not pour remaining solution from dip cup back into original container.

STORAGE INSTRUCTIONS

Store this product in a cool, dry area away from direct sunlight and heat to avoid deterioration. Keep containers closed to prevent contamination of this product. If frozen, separation may occur. Thaw completely and mix thoroughly before use.

NPE FREE

7751-0074-830 (Rev. 09-18)

GEA Farm Technologies, Inc. • 1880 Country Farm Drive • Naperville, IL 60563 U.S.A • www.gea.com • 800-323-1667 Made in U.S.A.

7751-0074-833

PACKAGE LABEL

Dairy Star®

ES 110

SANITIZING

IODINE TEAT DIP